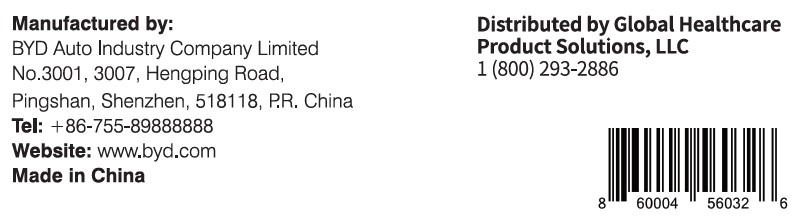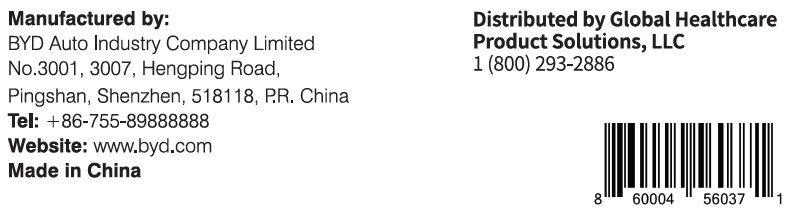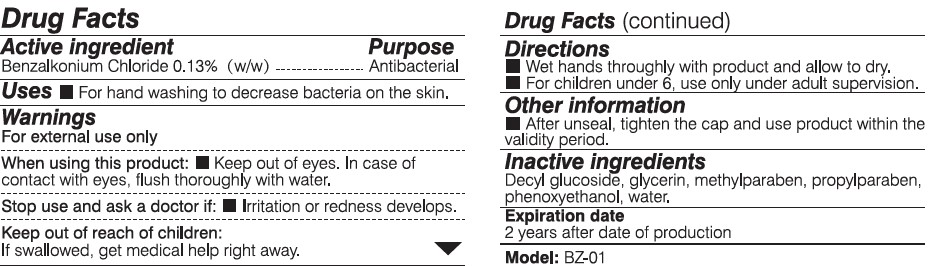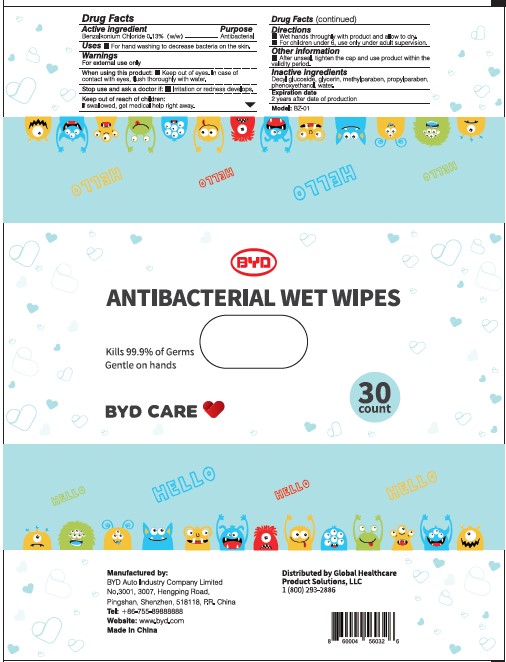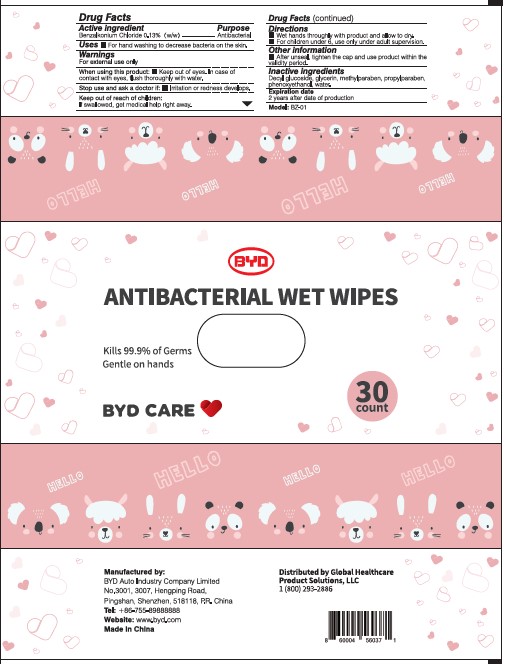 DRUG LABEL: BYD Antibacterial Wet Wipes (Children)
NDC: 75035-010 | Form: CLOTH
Manufacturer: BYD Automative Industry Co., Ltd.
Category: otc | Type: HUMAN OTC DRUG LABEL
Date: 20200920

ACTIVE INGREDIENTS: BENZALKONIUM CHLORIDE 0.13 g/100 g
INACTIVE INGREDIENTS: DECYL GLUCOSIDE 0.5 g/100 g; METHYLPARABEN 0.1 g/100 g; PHENOXYETHANOL 1 g/100 g; GLYCERIN 2 g/100 g; WATER 96.17 g/100 g; PROPYLPARABEN 0.1 g/100 g

Misc.

Manufactured by:

BYD Auto Industry Company Limited

No. 3001, 3007, Hengping Road,

Pingshan, Shenzhen, 518118, P.R. China

Tel: +86-755-89888888

Website: www.byd.com

Made in China

Distributed by Global Healthcare Product Solutions, LLC

1 (800) 293-2886

Active Ingredient:

Benzalkonium Chloride 0.13% (w/w)

Purpose:

Antibacterial

Uses:

For hand washing to decrease bacteria on the skin.

Warnings:

For external use only

When using this product:

Keep out of eyes. In case of contact with eyes, flush thoroughly with water.

When using this product:

Keep out of eyes. In case of contact with eyes, flush thoroughly with water.

Stop use and ask a doctor if:

Irritation or redness develops.

Keep out of reach of children:

If swallowed, get medical help right away.

Directions:

Wet hands thoroughly with product and allow to dry.

For children under 6, use only under adult supervision.

Other information:

After unseal, tighten the cap and use product within the validity period.

Inactive ingredients:

Decyl glucoside, glycerin, methylparaben, propylparaben, phenoxyethanol, water.